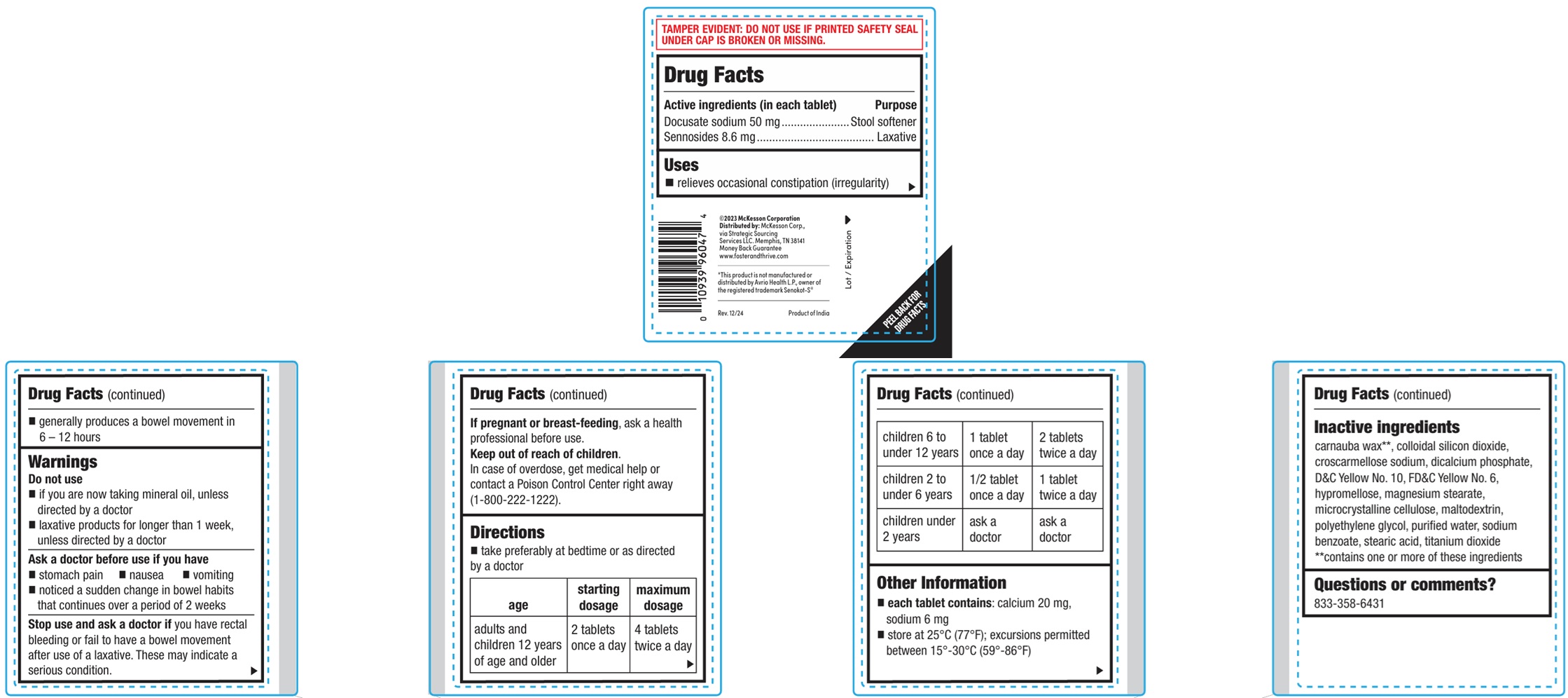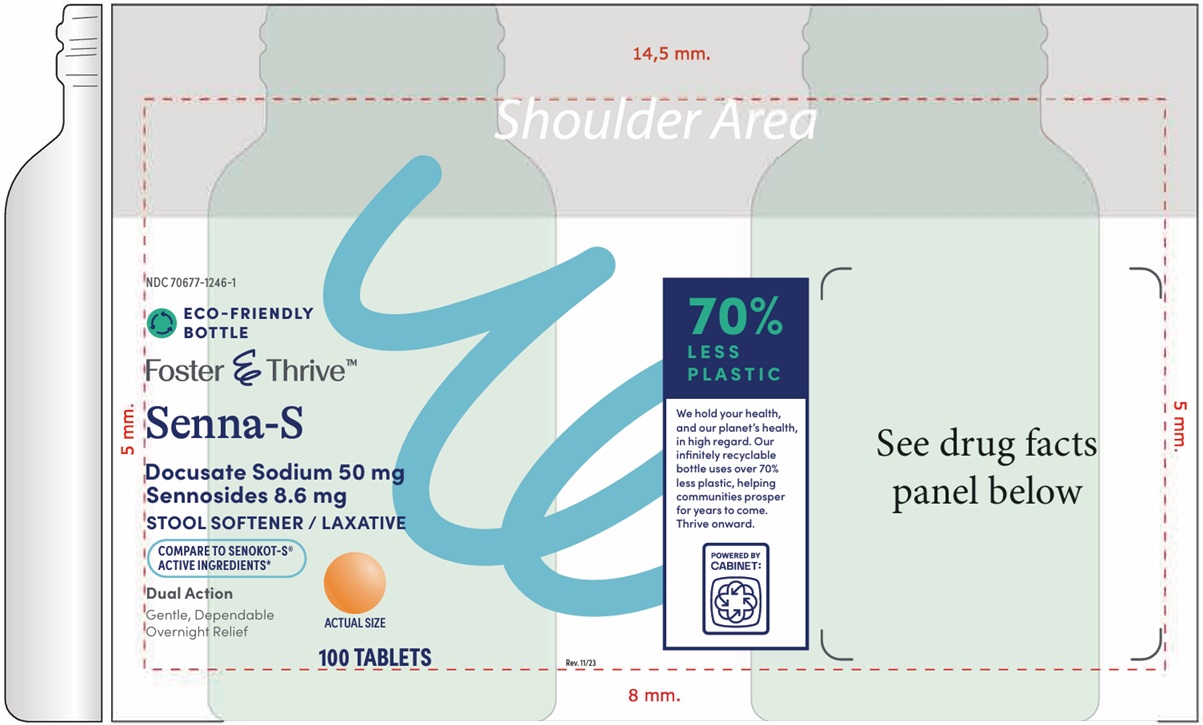 DRUG LABEL: SENNA-S
NDC: 70677-1246 | Form: TABLET, FILM COATED
Manufacturer: Strategic Sourcing Services, LLC
Category: otc | Type: HUMAN OTC DRUG LABEL
Date: 20260129

ACTIVE INGREDIENTS: DOCUSATE SODIUM 50 mg/1 1; SENNOSIDES 8.6 mg/1 1
INACTIVE INGREDIENTS: CARNAUBA WAX; SILICON DIOXIDE; CROSCARMELLOSE SODIUM; DIBASIC CALCIUM PHOSPHATE DIHYDRATE; D&C YELLOW NO. 10; FD&C YELLOW NO. 6; HYPROMELLOSES; MAGNESIUM STEARATE; MICROCRYSTALLINE CELLULOSE; MALTODEXTRIN; POLYETHYLENE GLYCOL, UNSPECIFIED; WATER; SODIUM BENZOATE; STEARIC ACID; TITANIUM DIOXIDE

Senna-S